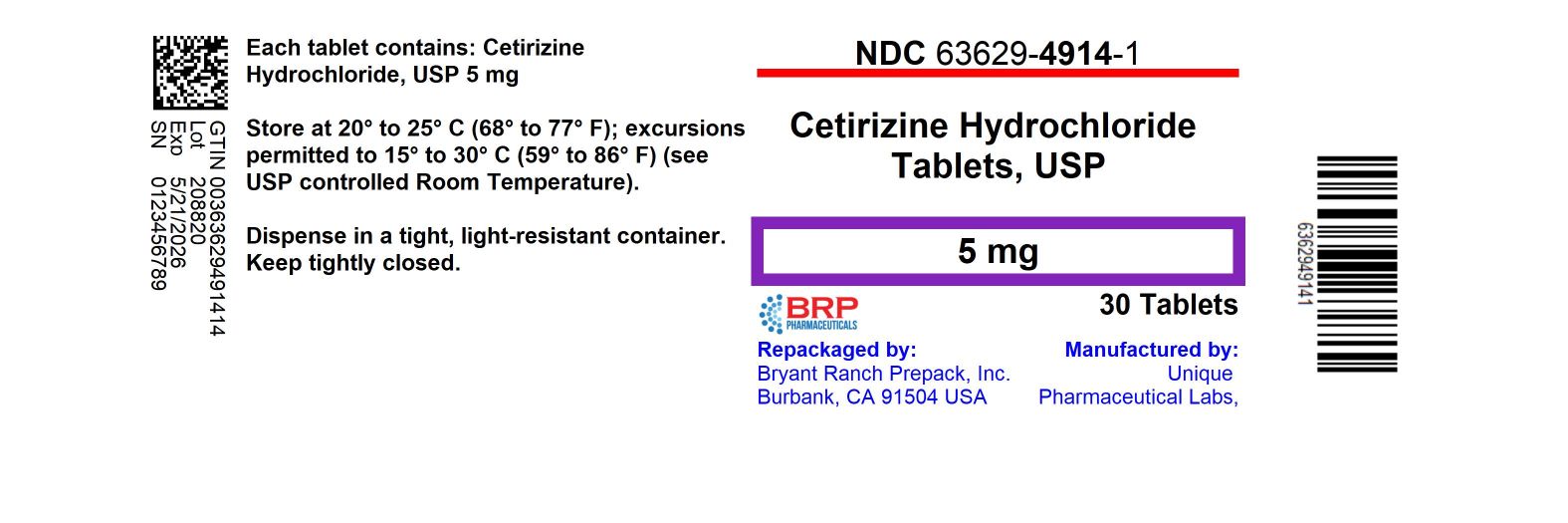 DRUG LABEL: Cetirizine Hydrochloride
NDC: 63629-4914 | Form: TABLET
Manufacturer: Bryant Ranch Prepack
Category: otc | Type: HUMAN OTC DRUG LABEL
Date: 20240521

ACTIVE INGREDIENTS: CETIRIZINE HYDROCHLORIDE 5 mg/1 1
INACTIVE INGREDIENTS: HYPROMELLOSE, UNSPECIFIED; LACTOSE, UNSPECIFIED FORM; MAGNESIUM STEARATE; STARCH, CORN; POLYETHYLENE GLYCOL, UNSPECIFIED; POVIDONE, UNSPECIFIED; TITANIUM DIOXIDE

Cetirizine Hydrochloride Tablets USP
5 mg, Allergy

Active Ingredient (in each tablet)

Cetirizine HCl USP 5 mg

Purpose

Antihistimine

Uses

Temporarily relieves these symptoms due to hay fever or other upper respiratory allergies:

- runny nose
- sneezing
- itchy, watery eyes
- itching of the nose or throat

Warnings:

Do Not Use if you have ever had an allergic reaction to this product or any of its ingredients or to an antihistamine containing hydroxyzine.

Ask a doctor before use if you have liver or kidney disease. Your doctor should determine if you need a different dose.

Ask a doctor or pharmacist before use if you are taking tranquilizers or sedatives.

When using this product

- drowsines may occur
- avoid alcoholic drinks
- alcohol, sedatives, and tranquilizers may increase drowsiness
- be careful when driving a motor vehicle or operating machinary.

Stop use and ask a doctor if an allergic reaction to this product occurs. Seek medical help right away.

If pregnant or breast-feeding:

- if breast-feeding: not recommended
- if pregnant: ask a health professional before use.

keep out of reach of children.

In case of overdose, get medical help or contact Poison Control Center right away. (1-800-222-1222)

Directions

Adults and children 6 years and over | 1 to 2 tablets once daily depending upon severity of symptoms; do not take more than 2 tablets in 24 hours
Adults 65 years and over | 1 tablet once a day; do not take more than 1 tablet in 24 hours
Children under 6 years of age | Ask a doctor
Consumers with liver or kidney disease | Ask a doctor

Other information:

Store at 20° to 25°C (68° to 77°F)

[See USP Controlled Room Temperature].

Inactive ingredients

hypromellose, lactose, magnesium stearate, maize starch, polyethylene glycol, povidone, titanium dioxide.

Questions?

Call 1-844-874-7464

Manufactured by:

Unique Pharmaceutical Labs,

(A Div. of J. B. Chemicals & Pharmaceuticals Ltd.),

Mumbai 400 030, India.

Distributed by:

Rising Pharma Holdings, Inc.
East Brunswick, NJ 08816

M.L. G/1430 Jul. 2020

129575

HOW SUPPLIED

Cetirizine Hydrochloride Tablets 5 mg

NDC: 63629-4914-1: 30 Tablets in a BOTTLE

Repackaged/Relabeled by:
Bryant Ranch Prepack, Inc.
Burbank, CA 91504

PACKAGE LABEL

Cetirizine Hydrochloride Tablets 5 mg